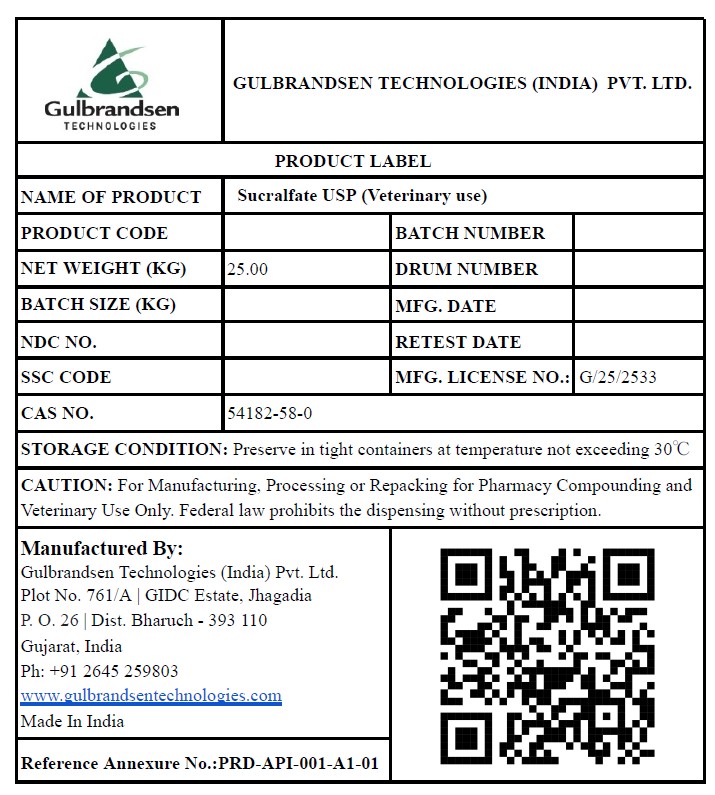 DRUG LABEL: SUCRALFATE
NDC: 31260-402 | Form: POWDER
Manufacturer: Gulbrandsen Technologies India Private Limited
Category: other | Type: BULK INGREDIENT - ANIMAL DRUG
Date: 20260224

ACTIVE INGREDIENTS: SUCRALFATE 1 kg/1 kg

SUCRALFATE USP

SUCRALFATE-USP-31260-402-01-25kg-LABEL

sucralfate-usp-25kg-label